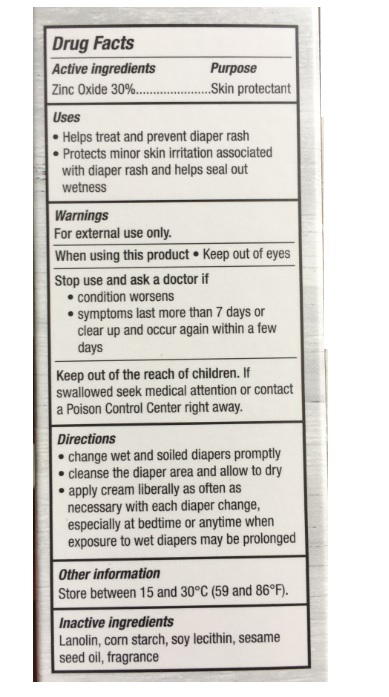 DRUG LABEL: Doctor Os Diaper Balm
NDC: 73570-001 | Form: OINTMENT
Manufacturer: Dr. O's Dermabalm, Llc
Category: otc | Type: HUMAN OTC DRUG LABEL
Date: 20241220

ACTIVE INGREDIENTS: ZINC OXIDE 30 g/100 g
INACTIVE INGREDIENTS: LANOLIN; STARCH, CORN; SOYBEAN LECITHIN; SESAME OIL

Doctor O's Diaper Balm

Active ingredients

Zinc Oxide 30%

Purpose

Skin protectant

Uses

- Helps treat and prevent diaper rash
- Protects minor skin irritation associated with diaper rash and helps seal out wetness

Warnings

For external use only.

When using this product • Keep out of eyes

Stop use and ask a doctor if

- condition worsens
- symptoms last more than 7 days or clear up and occur again within a few days

KEEP OUT OF REACH OF CHILDREN

Keep out of the reach of children. If swallowed seek medical attention or contact a Poison Control Center right away.

Directions

- change wet and soiled diapers promptly
- cleanse the diaper area and allow to dry
- apply ointment liberally as often as necessary with each diaper change, especially at bedtime or anytime when exposure to wet diapers may be prolonged

Other information

Store between 15 and 30°C (59 and 86°F).

Inactive ingredients

Lanolin, corn starch, soy lecithin, sesame seed oil, fragrance